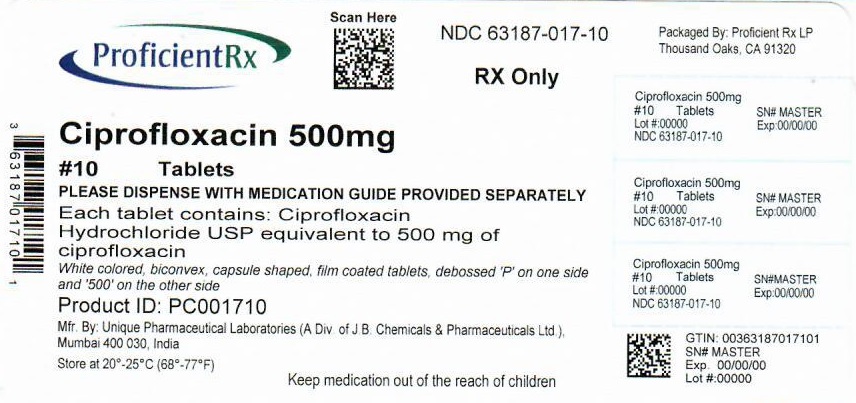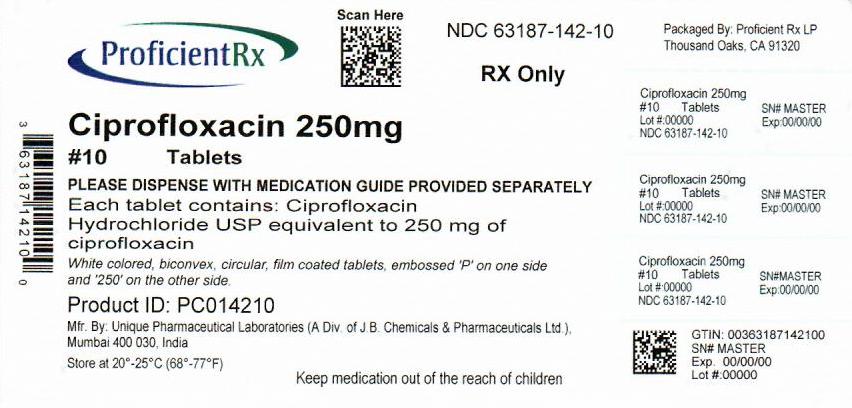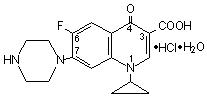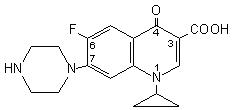 DRUG LABEL: ciprofloxacin
NDC: 63187-142 | Form: TABLET
Manufacturer: Proficient Rx LP
Category: prescription | Type: HUMAN PRESCRIPTION DRUG LABEL
Date: 20220601

ACTIVE INGREDIENTS: ciprofloxacin hydrochloride 250 mg/1 1
INACTIVE INGREDIENTS: STARCH, CORN; MICROCRYSTALLINE CELLULOSE; SILICON DIOXIDE; CROSPOVIDONE (120 .MU.M); MAGNESIUM STEARATE; HYPROMELLOSE, UNSPECIFIED; TITANIUM DIOXIDE; POLYETHYLENE GLYCOL, UNSPECIFIED; WATER

Ciprofloxacin Tablets 250 mg and 500 mg

WARNING:

Fluoroquinolones, including CIPROFLOXACIN TABLETS USP, 250 mg and 500 mg are
associated with an increased risk of tendinitis and tendon rupture in all ages. This risk is further
increased in older patients usually over 60 years of age, in patients taking corticosteroid drugs, and
in patients with kidney, heart or lung transplants (See WARNINGS).

To reduce the development of drug-resistant bacteria and maintain the effectiveness of Ciprofloxacin Tablets USP, 250 mg and 500 mg and other antibacterial drugs Ciprofloxacin Tablets USP, 250 mg and 500 mg should be used only to treat or prevent infections that are proven or strongly suspected to be caused by bacteria.

DESCRIPTION

Ciprofloxacin Hydrochloride Tablets USP, 250 mg and 500 mg are synthetic broad spectrum antimicrobial agents for oral administration. Ciprofloxacin hydrochloride, USP, a fluoroquinolone, is the monohydrochloride monohydrate salt of 1-cyclopropyl-6-fluoro-1, 4-dihydro-4-oxo-7-(1-piperazinyl)-3-quinolinecarboxylic acid. It is a faintly yellowish to light yellow crystalline substance with a molecular weight of 385.8. Its empirical formula is C17H18FN3O3•HCl•H2O and its chemical structure is as follows:

Ciprofloxacin is 1-cyclopropyl-6-fluoro-1,4-dihydro-4-oxo-7-(1-piperazinyl)-3-quinolinecarboxylic acid. Its empirical formula is C17H18FN3O3 and its molecular weight is 331.4. It is a faintly yellowish to light yellow crystalline substance and its chemical structure is as follows:

Ciprofloxacin Tablets USP are film-coated tablets and are available in 250 mg and 500 mg (ciprofloxacin equivalent) strengths. Ciprofloxacin Tablets are white to slightly yellowish. The inactive ingredients are pregelatinized starch, microcrystalline cellulose, colloidal silicon dioxide, crospovidone, magnesium stearate, hypromellose, titanium dioxide, polyethylene glycol and purified water.

CLINICAL PHARMACOLOGY

Absorption:

Ciprofloxacin given as an oral tablet is rapidly and well absorbed from the gastrointestinal tract after oral administration. The absolute bioavailability is approximately 70% with no substantial loss by first pass metabolism. Ciprofloxacin maximum serum concentrations and area under the curve are shown in the chart for the 250 mg to 1000 mg dose range.

Dose (mg) | Maximum Serum Concentrations (μg/mL) | Area Under Curve (AUC) (μg•hr/mL)
250 500 750 1000 | 1.2 2.4 4.3 5.4 | 4.8 11.6 20.2 30.8

Maximum serum concentrations are attained 1 to 2 hours after oral dosing. Mean concentrations 12 hours after dosing with 250 or 500 mg are 0.1 and 0.2 μg/mL, respectively. The serum elimination half-life in subjects with normal renal function is approximately 4 hours. Serum concentrations increase proportionately with doses up to 1000 mg.
A 500 mg oral dose given every 12 hours has been shown to produce an area under the serum concentration time curve (AUC) equivalent to that produced by an intravenous infusion of 400 mg ciprofloxacin given over 60 minutes every 12 hours. A 750 mg oral dose given every 12 hours has been shown to produce an AUC at steady-state equivalent to that produced by an intravenous infusion of 400 mg given over 60 minutes every 8 hours. A 750 mg oral dose results in a Cmax similar to that observed with a 400 mg I.V. dose. A 250 mg oral dose given every 12 hours produces an AUC equivalent to that produced by an infusion of 200 mg ciprofloxacin given every 12 hours.

Steady-state Pharmacokinetic Parameters
Following Multiple Oral and I.V. Doses
Parameters AUC (μg•hr/mL) Cmax (μg/mL) | 500 mg q12h, P.O. 13.7a 2.97 | 400 mg q12h, I.V. 12.7a 4.56 | 750 mg q12h, P.O. 31.6b 3.59 | 400 mg q8h, I.V. 32.9c 4.07

a AUC 0-12h
bAUC 24h=AUC0-12h x 2
cAUC 24h=AUC0-8h x 3

Distribution:

The binding of ciprofloxacin to serum proteins is 20 to 40% which is not likely to be high enough to cause significant protein binding interactions with other drugs.
After oral administration, ciprofloxacin is widely distributed throughout the body. Tissue concentrations often exceed serum concentrations in both men and women, particularly in genital tissue including the prostate. Ciprofloxacin is present in active form in the saliva, nasal and bronchial secretions, mucosa of the sinuses, sputum, skin blister fluid, lymph, peritoneal fluid, bile, and prostatic secretions. Ciprofloxacin has also been detected in lung, skin, fat, muscle, cartilage, and bone. The drug diffuses into the cerebrospinal fluid (CSF); however, CSF concentrations are generally less than 10% of peak serum concentrations. Low levels of the drug have been detected in the aqueous and vitreous humors of the eye.

Metabolism:

Four metabolites have been identified in human urine which together account for approximately 15% of an oral dose. The metabolites have antimicrobial activity, but are less active than unchanged ciprofloxacin. Ciprofloxacin is an inhibitor of human cytochrome P450 1A2 (CYP1A2) mediated metabolism. Coadministration of ciprofloxacin with other drugs primarily metabolized by CYP1A2 results in increased plasma concentrations of these drugs and could lead to clinically significant adverse events of the coadministered drug (see CONTRAINDICATIONS; WARNINGS; PRECAUTIONS: Drug Interactions).

Excretion:

The serum elimination half-life in subjects with normal renal function is approximately 4 hours. Approximately 40 to 50% of an orally administered dose is excreted in the urine as unchanged drug. After a 250 mg oral dose, urine concentrations of ciprofloxacin usually exceed 200 μg/mL during the first two hours and are approximately 30 μg/mL at 8 to 12 hours after dosing. The urinary excretion of ciprofloxacin is virtually complete within 24 hours after dosing. The renal clearance of ciprofloxacin, which is approximately 300 mL/minute, exceeds the normal glomerular filtration rate of 120 mL/minute. Thus, active tubular secretion would seem to play a significant role in its elimination. Co-administration of probenecid with ciprofloxacin results in about a 50% reduction in the ciprofloxacin renal clearance and a 50% increase in its concentration in the systemic circulation. Although bile concentrations of ciprofloxacin are several fold higher than serum concentrations after oral dosing, only a small amount of the dose administered is recovered from the bile as unchanged drug. An additional 1 to 2% of the dose is recovered from the bile in the form of metabolites. Approximately 20 to 35% of an oral dose is recovered from the feces within 5 days after dosing. This may arise from either biliary clearance or transintestinal elimination.

Drug-drug Interactions:

When Ciprofloxacin Tablets USP, 250 mg and 500 mg is given concomitantly with food, there is a delay in the absorption of the drug, resulting in peak concentrations that occur closer to 2 hours after dosing rather than 1 hour. The overall absorption of Ciprofloxacin Tablets USP, 250 mg and 500 mg however, is not substantially affected. Concurrent administration of antacids containing magnesium hydroxide or aluminum hydroxide may reduce the bioavailability of ciprofloxacin by as much as 90%. (See PRECAUTIONS.)
The serum concentrations of ciprofloxacin and metronidazole were not altered when these two drugs were given concomitantly.
Concomitant administration with tizanidine is contraindicated. (See CONTRAINDICATIONS.)
Concomitant administration of ciprofloxacin with theophylline decreases the clearance of theophylline resulting in elevated serum theophylline levels and increased risk of a patient developing CNS or other adverse reactions. Ciprofloxacin also decreases caffeine clearance and inhibits the formation of paraxanthine after caffeine administration. (See WARNINGS: PRECAUTIONS.)

Special Populations:

Pharmacokinetic studies of the oral (single dose) and intravenous (single and multiple dose) forms of ciprofloxacin indicate that plasma concentrations of ciprofloxacin are higher in elderly subjects (> 65 years) as compared to young adults. Although the Cmax is increased 16- 40%, the increase in mean AUC is approximately 30%, and can be at least partially attributed to decreased renal clearance in the elderly. Elimination half-life is only slightly (~20%) prolonged in the elderly. These differences are not considered clinically significant. (See PRECAUTIONS: Geriatric Use.)
In patients with reduced renal function, the half-life of ciprofloxacin is slightly prolonged. Dosage adjustments may be required. (See Error! Hyperlink reference not valid..)
In preliminary studies in patients with stable chronic liver cirrhosis, no significant changes in ciprofloxacin pharmacokinetics have been observed. The kinetics of ciprofloxacin in patients with acute hepatic insufficiency, however, have not been fully elucidated.

MICROBIOLOGY

Ciprofloxacin has in vitro activity against a wide range of gram-negative and gram-positive microorganisms. The bactericidal action of ciprofloxacin results from inhibition of the enzymes topoisomerase II (DNA gyrase) and topoisomerase IV, which are required for bacterial DNA replication, transcription, repair, and recombination. The mechanism of action of fluoroquinolones, including ciprofloxacin, is different from that of penicillins, cephalosporins, aminoglycosides, macrolides, and tetracyclines; therefore, microorganisms resistant to these classes of drugs may be susceptible to ciprofloxacin and other quinolones. There is no known cross-resistance between ciprofloxacin and other classes of antimicrobials. In vitro resistance to ciprofloxacin develops slowly by multiple step mutations.
Ciprofloxacin is slightly less active when tested at acidic pH. The inoculum size has little effect when tested in vitro. The minimal bactericidal concentration (MBC) generally does not exceed the minimal inhibitory concentration (MIC) by more than a factor of 2.
Ciprofloxacin has been shown to be active against most strains of the following microorganisms, both in vitro and in clinical infections as described in the INDICATIONS AND USAGE section of the package insert for Ciprofloxacin Hydrochloride Tablets USP, 250mg, 500mg and 750mg.

Aerobic gram-positive microorganisms

Enterococcus faecalis (Many strains are only moderately susceptible.)
Staphylococcus aureus (methicillin-susceptible strains only)
Staphylococcus epidermidis (methicillin-susceptible strains only)
Staphylococcus saprophyticus
Streptococcus pneumoniae (penicillin-susceptible strains only)
Streptococcus pyogenes

Aerobic gram-negative microorganisms

Campylobacter jejuni Proteus mirabilis
Citrobacter diversus Proteus vulgaris
Citrobacter freundii Providencia rettgeri
Enterobacter cloacae Providencia stuartii
Escherichia coli Pseudomonas aeruginosa
Haemophilus influenzae Salmonella typhi
Haemophilus parainfluenzae Serratia marcescens
Klebsiella pneumoniae Shigella boydii
Moraxella catarrhalis Shigella dysenteriae
Morganella morganii Shigella flexneri
Neisseria gonorrhoeae Shigella sonnei
Ciprofloxacin has been shown to be active against Bacillus anthracis both in vitro and by use of serum levels as a surrogate marker (see INDICATIONS AND USAGE and INHALATIONAL ANTHRAX – ADDITIONAL INFORMATION).
The following in vitro data are available, but their clinical significance is unknown.
Ciprofloxacin exhibits in vitro minimum inhibitory concentrations (MICs) of 1 μg/mL or less against most (≥ 90%) strains of the following microorganisms; however, the safety and effectiveness of ciprofloxacin in treating clinical infections due to these microorganisms have not been established in adequate and well-controlled clinical trials.

Aerobic gram-positive microorganisms

Staphylococcus haemolyticus
Staphylococcus hominis
Streptococcus pneumoniae (penicillin-resistant strains only)

Aerobic gram-negative microorganisms

Acinetobacter Iwoffii Pasteurella multocida
Aeromonas hydrophila Salmonella enteritidis
Edwardsiella tarda Vibrio cholerae
Enterobacter aerogenes Vibrio parahaemolyticus
Klebsiella oxytoca Vibrio vulnificus
Legionella pneumophila Yersinia enterocolitica
Most strains of Burkholderia cepacia and some strains of Stenotrophomonas maltophilia are resistant to ciprofloxacin as are most anaerobic bacteria, including Bacteroides fragilis and Clostridium difficile.

Susceptibility Tests

Dilution Techniques:

Quantitative methods are used to determine antimicrobial minimum inhibitory concentrations (MICs). These MICs provide estimates of the susceptibility of bacteria to antimicrobial compounds. The MICs should be determined using a standardized procedure. Standardized procedures are based on a dilution method^1 (broth or agar) or equivalent with standardized inoculum concentrations and standardized concentrations of ciprofloxacin powder. The MIC values should be interpreted according to the following criteria:
For testing aerobic microorganisms other than Haemophilus influenzae , Haemophilus parainfluenzae, and Neisseria gonorrhoeaea:

MIC (μg/mL) | Interpretation
≤ 1 | Susceptible (S)
2 | Intermediate (I)
≥ 4 | Resistant (R)

a These interpretive standards are applicable only to broth microdilution susceptibility tests with streptococci using cation-adjusted Mueller-Hinton broth with 2-5% lysed horse blood.
For testing Haemophilus influenzae and Haemophilus parainfluenzaeb:

MIC (μg/mL) | Interpretation
≤ 1 | Susceptible (S)

b This interpretive standard is applicable only to broth microdilution susceptibility tests with Haemophilus influenzae and Haemophilus parainfluenzae using Haemophilus Test Medium.^1
The current absence of data on resistant strains precludes defining any results other than “Susceptible”. Strains yielding MIC results suggestive of a “nonsusceptible” category should be submitted to a reference laboratory for further testing.
For testing Neisseria gonorrhoeaec:

MIC (μg/mL) | Interpretation
≤ 0.06 | Susceptible (S)
0.12 – 0.5 | Intermediate (I)
≥ 1 | Resistant (R)

c This interpretive standard is applicable only to agar dilution test with GC agar base and 1% defined growth supplement.
A report of “Susceptible” indicates that the pathogen is likely to be inhibited if the antimicrobial compound in the blood reaches the concentrations usually achievable. A report of “Intermediate” indicates that the result should be considered equivocal, and, if the microorganism is not fully susceptible to alternative, clinically feasible drugs, the test should be repeated. This category implies possible clinical applicability in body sites where the drug is physiologically concentrated or in situations where high dosage of drug can be used. This category also provides a buffer zone, which prevents small uncontrolled technical factors from causing major discrepancies in interpretation. A report of “Resistant” indicates that the pathogen is not likely to be inhibited if the antimicrobial compound in the blood reaches the concentrations usually achievable; other therapy should be selected.
Standardized susceptibility test procedures require the use of laboratory control microorganisms to control the technical aspects of the laboratory procedures. Standard ciprofloxacin powder should provide the following MIC values:

Organism |  | MIC (μg/mL)
E. faecalis | ATCC 29212 | 0.25 – 2
E. coli | ATCC 25922 | 0.004 – 0.015
H. influenzaea | ATCC 49247 | 0.004 – 0.03
P. aeruginosa | ATCC 27853 | 0.25 – 1.0
S. aureus | ATCC 29213 | 0.12 – 0.5
C. jejunib | ATCC 33560 | 0.06 – 0.25 and 0.03 – 0.12
N. gonorrhoeaec | ATCC 49226 | 0.001– 0.008

a This quality control range is applicable to only H. influenzae ATCC 49247 tested by a broth microdilution procedure using Haemophilus Test Medium (HTM)^1.
b C. jejuni ATCC 33560 tested by broth microdilution procedure using cation adjusted Mueller Hinton broth with 2.5-5% lysed horse blood in a microaerophilic environment at 36-37°C for 48 hours and for 42°C at 24 hours^2, respectively.
c N. gonorrhoeae ATCC 49226 tested by agar dilution procedure using GC agar and 1% defined growth supplement in a 5% CO2 environment at 35-37°C for 20-24 hours^3.

Diffusion Techniques:

Quantitative methods that require measurement of zone diameters also provide reproducible estimates of the susceptibility of bacteria to antimicrobial compounds. One such standardized procedure^3 requires the use of standardized inoculum concentrations. This procedure uses paper disks impregnated with 5-μg ciprofloxacin to test the susceptibility of microorganisms to ciprofloxacin.
Reports from the laboratory providing results of the standard single-disk susceptibility test with a 5-μg ciprofloxacin disk should be interpreted according to the following criteria:
For testing Enterobacteriaceae, Enterococcus faecalis, methicillin-susceptible Staphylococcus species, penicillin-susceptible Streptococcus pneumoniae, Streptococcus pyogenes, and Pseudomonas aeruginosaa:

Zone Diameter (mm) | Interpretation
≥ 21 | Susceptible (S)
16 – 20 | Intermediate (I)
≤ 15 | Resistant (R)

a These zone diameter standards are applicable only to tests performed for streptococci using Mueller-Hinton agar supplemented with 5% sheep blood incubated in 5% CO2.
For testing Haemophilus influenzae and Haemophilus parainfluenzaeb:

Zone Diameter (mm) | Interpretation
≥ 21 | Susceptible (S)

b This zone diameter standard is applicable only to tests with Haemophilus influenzae and Haemophilus parainfluenzae using Haemophilus Test Medium (HTM).^3
The current absence of data on resistant strains precludes defining any results other than “Susceptible”. Strains yielding zone diameter results suggestive of a “nonsusceptible” category should be submitted to a reference laboratory for further testing.
For testing Neisseria gonorrhoeaec:

Zone Diameter (mm) | Interpretation
≥41 | Susceptible (S)
28 – 40 | Intermediate (I)
≤ 27 | Resistant (R)

c This zone diameter standard is applicable only to disk diffusion tests with GC agar base and 1% defined growth supplement.
Interpretation should be as stated above for results using dilution techniques. Interpretation involves correlation of the diameter obtained in the disk test with the MIC for ciprofloxacin.
As with standardized dilution techniques, diffusion methods require the use of laboratory control microorganisms that are used to control the technical aspects of the laboratory procedures. For the diffusion technique, the 5-μg ciprofloxacin disk should provide the following zone diameters in these laboratory test quality control strains:

Organism |  | Zone Diameter (mm)
E. coli | ATCC 25922 | 30-40
H. influenzaea | ATCC 49247 | 34-42
N. gonorrhoeaeb | ATCC 49226 | 48-58
P. aeruginosa | ATCC 27853 | 25-33
S. aureus | ATCC 25923 | 22-30

a These quality control limits are applicable to only H. influenzae ATCC 49247 testing using Haemophilus Test Medium (HTM).^3
b These quality control limits are applicable only to tests conducted with N. gonorrhoeae ATCC 49226 performed by disk diffusion using GC agar base and 1% defined growth supplement.

INDICATIONS AND USAGE

Ciprofloxacin Tablets USP, 250 mg and 500 mg is indicated for the treatment of infections caused by susceptible strains of the designated microorganisms in the conditions and patient populations listed below. Please see Error! Hyperlink reference not valid. for specific recommendations.

Adult Patients:

Urinary Tract Infections caused by Escherichia coli, Klebsiella pneumoniae, Enterobacter cloacae, Serratia marcescens, Proteus mirabilis, Providencia rettgeri, Morganella morganii, Citrobacter diversus, Citrobacter freundii, Pseudomonas aeruginosa, methicillin-susceptible Staphylococcus epidermidis, Staphylococcus saprophyticus, or Enterococcus faecalis.
Acute Uncomplicated Cystitis in females caused by Escherichia coli or Staphylococcus saprophyticus.
Chronic Bacterial Prostatitis caused by Escherichia coli or Proteus mirabilis.
Lower Respiratory Tract Infections caused by Escherichia coli, Klebsiella pneumoniae, Enterobacter cloacae, Proteus mirabilis, Pseudomonas aeruginosa, Haemophilus influenzae, Haemophilus parainfluenzae, or penicillin-susceptible Streptococcus pneumoniae. Also, Moraxella catarrhalis for the treatment of acute exacerbations of chronic bronchitis.
NOTE: Although effective in clinical trials, ciprofloxacin is not a drug of first choice in the treatment of presumed or confirmed pneumonia secondary to Streptococcus pneumoniae.
Acute Sinusitis caused by Haemophilus influenzae, penicillin-susceptible Streptococcus pneumoniae, or Moraxella catarrhalis.
Skin and Skin Structure Infections caused by Escherichia coli, Klebsiella pneumoniae, Enterobacter cloacae, Proteus mirabilis, Proteus vulgaris, Providencia stuartii, Morganella morganii, Citrobacter freundii, Pseudomonas aeruginosa, methicillin-susceptible Staphylococcus aureus, methicillin-susceptible Staphylococcus epidermidis, or Streptococcus pyogenes.
Bone and Joint Infections caused by Enterobacter cloacae, Serratia marcescens, or Pseudomonas aeruginosa.
Complicated Intra-Abdominal Infections (used in combination with metronidazole) caused by Escherichia coli, Pseudomonas aeruginosa, Proteus mirabilis, Klebsiella pneumoniae, or Bacteroides fragilis.
Infectious Diarrhea caused by Escherichia coli (enterotoxigenic strains), Campylobacter jejuni, Shigella boydii†, Shigella dysenteriae, Shigella flexneri or Shigella sonnei† when antibacterial therapy is indicated.
Typhoid Fever (Enteric Fever) caused by Salmonella typhi.
NOTE: The efficacy of ciprofloxacin in the eradication of the chronic typhoid carrier state has not been demonstrated.
Uncomplicated cervical and urethral gonorrhea due to Neisseria gonorrhoeae.

Pediatric patients (1 to 17 years of age):

Complicated Urinary Tract Infections and Pyelonephritis due to Escherichia coli.
NOTE: Although effective in clinical trials, ciprofloxacin is not a drug of first choice in the pediatric population due to an increased incidence of adverse events compared to controls, including events related to joints and/or surrounding tissues. (See WARNINGS, PRECAUTIONS, Pediatric Use, ADVERSE REACTIONS and CLINICAL STUDIES.)
Ciprofloxacin, like other fluoroquinolones, is associated with arthropathy and histopathological changes in weight-bearing joints of juvenile animals. (See ANIMAL PHARMACOLOGY.)

Adult and Pediatric Patients:

Inhalational anthrax (post-exposure): To reduce the incidence or progression of disease following exposure to aerosolized Bacillus anthracis.
Ciprofloxacin serum concentrations achieved in humans served as a surrogate endpoint reasonably likely to predict clinical benefit and provided the initial basis for approval of this indication.^5 Supportive clinical information for ciprofloxacin for anthrax post-exposure prophylaxis was obtained during the anthrax bioterror attacks of October 2001. (See also, INHALATIONAL ANTHRAX – ADDITIONAL INFORMATION).
†Although treatment of infections due to this organism in this organ system demonstrated a clinically significant outcome, efficacy was studied in fewer than 10 patients.
If anaerobic organisms are suspected of contributing to the infection, appropriate therapy should be administered. Appropriate culture and susceptibility tests should be performed before treatment in order to isolate and identify organisms causing infection and to determine their susceptibility to ciprofloxacin. Therapy with Ciprofloxacin Tablets USP, 250 mg and 500 mg and may be initiated before results of these tests are known; once results become available appropriate therapy should be continued. As with other drugs, some strains of Pseudomonas aeruginosa may develop resistance fairly rapidly during treatment with ciprofloxacin. Culture and susceptibility testing performed periodically during therapy will provide information not only on the therapeutic effect of the antimicrobial agent but also on the possible emergence of bacterial resistance.
To reduce the development of drug-resistant bacteria and maintain the effectiveness of Ciprofloxacin Tablets USP, 250 mg and 500 mg and other antibacterial drugs, Ciprofloxacin Tablets USP, 250 mg and 500 mg should be used only to treat or prevent infections that are proven or strongly suspected to be caused by susceptible bacteria. When culture and susceptibility information are available, they should be considered in selecting or modifying antibacterial therapy. In the absence of such data, local epidemiology and susceptibility patterns may contribute to the empiric selection of therapy.

CONTRAINDICATIONS

Ciprofloxacin is contraindicated in persons with a history of hypersensitivity to ciprofloxacin, any member of the quinolone class of antimicrobial agents, or any of the product components.
Concomitant administration with tizanidine is contraindicated. (See PRECAUTIONS: Drug Interactions.)

WARNINGS

Tendinopathy and Tendon Rupture:

Fluoroquinolones, including Ciprofloxacin Tablets USP, 250 mg and 500 mg are associated with an increased risk of tendinitis and tendon rupture in all ages. This adverse reaction most frequently involves the Achilles tendon, and rupture of the Achilles tendon may require surgical repair. Tendinitis and tendon rupture in the rotator cuff (the shoulder), the hand, the biceps, the thumb, and other tendon sites have also been reported. The risk of developing fluoroquinolone-associated tendinitis and tendon rupture is further increased in older patients usually over 60 years of age, in patients taking corticosteroid drugs, and in patients with kidney, heart or lung transplants. Factors, in addition to age and corticosteroid use, that may independently increase the risk of tendon rupture include strenuous physical activity, renal failure, and previous tendon disorders such as rheumatoid arthritis. Tendinitis and tendon rupture have also occurred in patients taking fluoroquinolones who do not have the above risk factors. Tendon rupture can occur during or after completion of therapy; cases occurring up to several months after completion of therapy have been reported. Ciprofloxacin Tablets USP, 250 mg and 500 mg should be discontinued if the patient experiences pain, swelling, inflammation or rupture of a tendon. Patients should be advised to rest at the first sign of tendinitis or tendon rupture, and to contact their healthcare provider regarding changing to a non-quinolone antimicrobial drug.

Pregnant Women:

THE SAFETY AND EFFECTIVENESS OF CIPROFLOXACIN IN PREGNANT AND LACTATING WOMEN HAVE NOT BEEN ESTABLISHED. (See PRECAUTIONS: Pregnancy, and Nursing Mothers subsections.)

Pediatrics:

Ciprofloxacin should be used in pediatric patients (less than 18 years of age) only for infections listed in the INDICATIONS AND USAGE section. An increased incidence of adverse events compared to controls, including events related to joints and/or surrounding tissues, has been observed. (See ADVERSE REACTIONS.)
In pre-clinical studies, oral administration of ciprofloxacin caused lameness in immature dogs. Histopathological examination of the weight-bearing joints of these dogs revealed permanent lesions of the cartilage. Related quinolone-class drugs also produce erosions of cartilage of weight-bearing joints and other signs of arthropathy in immature animals of various species. (See ANIMAL PHARMACOLOGY.)

Cytochrome P450 (CYP450):

Ciprofloxacin is an inhibitor of the hepatic CYP1A2 enzyme pathway. Coadministration of ciprofloxacin and other drugs primarily metabolized by CYP1A2 (e.g. theophylline, methylxanthines, tizanidine) results in increased plasma concentrations of the coadministered drug and could lead to clinically significant pharmacodynamic side effects of the coadministered drug.

Central Nervous System Disorders:

Convulsions, increased intracranial pressure, and toxic psychosis have been reported in patients receiving quinolones, including ciprofloxacin. Ciprofloxacin may also cause central nervous system (CNS) events including: dizziness, confusion, tremors, hallucinations, depression, and, rarely, suicidal thoughts or acts. These reactions may occur following the first dose. If these reactions occur in patients receiving ciprofloxacin, the drug should be discontinued and appropriate measures instituted. As with all quinolones, ciprofloxacin should be used with caution in patients with known or suspected CNS disorders that may predispose to seizures or lower the seizure threshold (e.g. severe cerebral arteriosclerosis, epilepsy), or in the presence of other risk factors that may predispose to seizures or lower the seizure threshold (e.g. certain drug therapy, renal dysfunction). (See PRECAUTIONS: General, Information for Patients, Drug Interactions and ADVERSE REACTIONS.)

Theophylline:

SERIOUS AND FATAL REACTIONS HAVE BEEN REPORTED IN PATIENTS RECEIVING CONCURRENT ADMINISTRATION OF CIPROFLOXACIN AND THEOPHYLLINE. These reactions have included cardiac arrest, seizure, status epilepticus, and respiratory failure. Although similar serious adverse effects have been reported in patients receiving theophylline alone, the possibility that these reactions may be potentiated by ciprofloxacin cannot be eliminated. If concomitant use cannot be avoided, serum levels of theophylline should be monitored and dosage adjustments made as appropriate.

Hypersensitivity Reactions:

Serious and occasionally fatal hypersensitivity (anaphylactic) reactions, some following the first dose, have been reported in patients receiving quinolone therapy. Some reactions were accompanied by cardiovascular collapse, loss of consciousness, tingling, pharyngeal or facial edema, dyspnea, urticaria, and itching. Only a few patients had a history of hypersensitivity reactions. Serious anaphylactic reactions require immediate emergency treatment with epinephrine. Oxygen, intravenous steroids, and airway management, including intubation, should be administered as indicated.
Other serious and sometimes fatal events, some due to hypersensitivity, and some due to uncertain etiology, have been reported rarely in patients receiving therapy with quinolones, including ciprofloxacin. These events may be severe and generally occur following the administration of multiple doses. Clinical manifestations may include one or more of the following:

- fever, rash, or severe dermatologic reactions (e.g., toxic epidermal necrolysis, Stevens-Johnson syndrome);
- vasculitis; arthralgia; myalgia; serum sickness;
- allergic pneumonitis;
- interstitial nephritis; acute renal insufficiency or failure;
- hepatitis; jaundice; acute hepatic necrosis or failure;
- anemia, including hemolytic and aplastic; thrombocytopenia, including thrombotic thrombocytopenic purpura; leukopenia; agranulocytosis; pancytopenia; and/or other hematologic abnormalities.

The drug should be discontinued immediately at the first appearance of a skin rash, jaundice, or any other sign of hypersensitivity and supportive measures instituted (See PRECAUTIONS: Information for Patients and ADVERSE REACTIONS).

Pseudomembranous Colitis:

Clostridium difficile associated diarrhea (CDAD) has been reported with use of nearly all antibacterial agents, including Ciprofloxacin Tablets USP, 250 mg and 500 mg and may range in severity from mild diarrhea to fatal colitis. Treatment with antibacterial agents alters the normal flora of the colon leading to overgrowth of C. difficile.

C. difficile produces toxins A and B which contribute to the development of CDAD. Hypertoxin producing strains of C. difficile cause increased morbidity and mortality, as these infections can be refractory to antimicrobial therapy and may require colectomy. CDAD must be considered in all patients who present with diarrhea following antibiotic use. Careful medical history is necessary since CDAD has been reported to occur over two months after the administration of antibacterial agents.

If CDAD is suspected or confirmed, ongoing antibiotic use not directed against C. difficile may need to be discontinued. Appropriate fluid and electrolyte management, protein supplementation, antibiotic treatment of C. difficile, and surgical evaluation should be instituted as clinically indicated.

Peripheral neuropathy:

Rare cases of sensory or sensorimotor axonal polyneuropathy affecting small and/or large axons resulting in paresthesias, hypoesthesias, dysesthesias and weakness have been reported in patients receiving quinolones, including ciprofloxacin. Ciprofloxacin should be discontinued if the patient experiences symptoms of neuropathy including pain, burning, tingling, numbness, and/or weakness, or is found to have deficits in light touch, pain, temperature, position sense, vibratory sensation, and/or motor strength in order to prevent the development of an irreversible condition.

Syphilis:

Ciprofloxacin has not been shown to be effective in the treatment of syphilis. Antimicrobial agents used in high dose for short periods of time to treat gonorrhea may mask or delay the symptoms of incubating syphilis. All patients with gonorrhea should have a serologic test for syphilis at the time of diagnosis. Patients treated with ciprofloxacin should have a follow-up serologic test for syphilis after three months.

PRECAUTIONS

General:

Crystals of ciprofloxacin have been observed rarely in the urine of human subjects but more frequently in the urine of laboratory animals, which is usually alkaline. (See ANIMAL PHARMACOLOGY.) Crystalluria related to ciprofloxacin has been reported only rarely in humans because human urine is usually acidic. Alkalinity of the urine should be avoided in patients receiving ciprofloxacin. Patients should be well hydrated to prevent the formation of highly concentrated urine.
Central Nervous System:
Quinolones, including ciprofloxacin, may also cause central nervous system (CNS) events, including: nervousness, agitation, insomnia, anxiety, nightmares or paranoia. (See WARNINGS, Information for Patients, and Drug Interactions.)
Renal Impairment:
Alteration of the dosage regimen is necessary for patients with impairment of renal function. (See Error! Hyperlink reference not valid..)
Photosensitivity/Phototoxicity:
Moderate to severe photosensitivity/phototoxicity reactions, the latter of which may manifest as exaggerated sunburn reactions (e.g., burning, erythema, exudation, vesicles, blistering, edema) involving areas exposed to light (typically the face, “V” area of the neck, extensor surfaces of the forearms, dorsa of the hands), can be associated with the use of quinolones after sun or UV light exposure. Therefore, excessive exposure to these sources of light should be avoided. Drug therapy should be discontinued if phototoxicity occurs (See ADVERSE REACTIONS/Post-Marketing Adverse Events).
As with any potent drug, periodic assessment of organ system functions, including renal, hepatic, and hematopoietic function, is advisable during prolonged therapy.
Prescribing Ciprofloxacin Tablets USP, 250 mg and 500 mg in the absence of a proven or strongly suspected bacterial infection or a prophylactic indication is unlikely to provide benefit to the patient and increases the risk of the development of drug-resistant bacteria.

Information for Patients:

Patients should be advised:

- to contact their healthcare provider if they experience pain, swelling, or inflammation of a tendon, or weakness or inability to use one of their joints; rest and refrain from exercise; and discontinue Ciprofloxacin Tablets USP, 250 mg and 500 mg treatment. The risk of severe tendon disorder with fluoroquinolones is higher in older patients usually over 60 years of age, in patients taking corticosteroid drugs, and in patients with kidney, heart or lung transplants.
- that antibacterial drugs including Ciprofloxacin Tablets USP, 250 mg and 500 mg should only be used to treat bacterial infections. They do not treat viral infections (e.g., the common cold). When Ciprofloxacin Tablets USP, 250 mg and 500 mg is prescribed to treat a bacterial infection, patients should be told that although it is common to feel better early in the course of therapy, the medication should be taken exactly as directed. Skipping doses or not completing the full course of therapy may (1) decrease the effectiveness of the immediate treatment and (2) increase the likelihood that bacteria will develop resistance and will not be treatable by Ciprofloxacin Tablets USP, 250 mg and 500 mg or other antibacterial drugs in the future.
- that ciprofloxacin may be taken with or without meals and to drink fluids liberally. As with other quinolones, concurrent administration of ciprofloxacin with magnesium/aluminum antacids, or sucralfate, Videx® (didanosine) chewable/buffered tablets or pediatric powder, other highly buffered drugs, or with other products containing calcium, iron or zinc should be avoided. Ciprofloxacin may be taken two hours before or six hours after taking these products. Ciprofloxacin should not be taken with dairy products (like milk or yogurt) or calcium-fortified juices alone since absorption of ciprofloxacin may be significantly reduced; however, ciprofloxacin may be taken with a meal that contains these products.
- that ciprofloxacin may be associated with hypersensitivity reactions, even following a single dose, and to discontinue the drug at the first sign of a skin rash or other allergic reaction.
- that photosensitivity/phototoxicity has been reported in patients receiving quinolones. Patients should minimize or avoid exposure to natural or artificial sunlight (tanning beds or UVA/B treatment) while taking quinolones. If patients need to be outdoors while using quinolones, they should wear loose-fitting clothes that protect skin from sun exposure and discuss other sun protection measures with their physician. If a sunburn-like reaction or skin eruption occurs, patients should contact their physician.
- that peripheral neuropathies have been associated with ciprofloxacin use. If symptoms of peripheral neuropathy including pain, burning, tingling, numbness and/or weakness develop, they should discontinue treatment and contact their physicians.
- that ciprofloxacin may cause dizziness and lightheadedness; therefore, patients should know how they react to this drug before they operate an automobile or machinery or engage in activities requiring mental alertness or coordination.
- that ciprofloxacin increases the effects of tizanidine (Zanaflex®). Patients should not use ciprofloxacin if they are already taking tizanidine.
- that ciprofloxacin may increase the effects of theophylline and caffeine. There is a possibility of caffeine accumulation when products containing caffeine are consumed while taking quinolones.
- that convulsions have been reported in patients receiving quinolones, including ciprofloxacin, and to notify their physician before taking this drug if there is a history of this condition.
- that ciprofloxacin has been associated with an increased rate of adverse events involving joints and surrounding tissue structures (like tendons) in pediatric patients (less than 18 years of age). Parents should inform their child’s physician if the child has a history of joint-related problems before taking this drug. Parents of pediatric patients should also notify their child’s physician of any joint-related problems that occur during or following ciprofloxacin therapy. (See WARNINGS, PRECAUTIONS, Pediatric Use and ADVERSE REACTIONS.)
- that diarrhea is a common problem caused by antibiotics which usually ends when the antibiotic is discontinued. Sometimes after starting treatment with antibiotics, patients can develop watery and bloody stools (with or without stomach cramps and fever) even as late as two or more months after having taken the last dose of the antibiotic. If this occurs, patients should contact their physician as soon as possible.

Drug Interactions:

In a pharmacokinetic study, systemic exposure of tizanidine (4 mg single dose) was significantly increased (Cmax 7-fold, AUC 10-fold) when the drug was given concomitantly with ciprofloxacin (500 mg bid for 3 days). The hypotensive and sedative effects of tizanidine were also potentiated. Concomitant administration of tizanidine and ciprofloxacin is contraindicated.
As with some other quinolones, concurrent administration of ciprofloxacin with theophylline may lead to elevated serum concentrations of theophylline and prolongation of its elimination half-life. This may result in increased risk of theophylline-related adverse reactions. (See WARNINGS.) If concomitant use cannot be avoided, serum levels of theophylline should be monitored and dosage adjustments made as appropriate.
Some quinolones, including ciprofloxacin, have also been shown to interfere with the metabolism of caffeine. This may lead to reduced clearance of caffeine and a prolongation of its serum half-life.
Concurrent administration of a quinolone, including ciprofloxacin, with multivalent cation-containing products such as magnesium/aluminum antacids, sucralfate, Videx® (didanosine) chewable/buffered tablets or pediatric powder, other highly buffered drugs, or products containing calcium, iron, or zinc may substantially decrease its absorption, resulting in serum and urine levels considerably lower than desired. (See Error! Hyperlink reference not valid. for concurrent administration of these agents with ciprofloxacin.)
Histamine H2-receptor antagonists appear to have no significant effect on the bioavailability of ciprofloxacin.
Altered serum levels of phenytoin (increased and decreased) have been reported in patients receiving concomitant ciprofloxacin.
The concomitant administration of ciprofloxacin with the sulfonylurea glyburide has, on rare occasions, resulted in severe hypoglycemia.
Some quinolones, including ciprofloxacin, have been associated with transient elevations in serum creatinine in patients receiving cyclosporine concomitantly.
Quinolones, including ciprofloxacin, have been reported to enhance the effects of the oral anticoagulant warfarin or its derivatives. When these products are administered concomitantly, prothrombin time or other suitable coagulation tests should be closely monitored.
Probenecid interferes with renal tubular secretion of ciprofloxacin and produces an increase in the level of ciprofloxacin in the serum. This should be considered if patients are receiving both drugs concomitantly.
Renal tubular transport of methotrexate may be inhibited by concomitant administration of ciprofloxacin potentially leading to increased plasma levels of methotrexate. This might increase the risk of methotrexate associated toxic reactions. Therefore, patients under methotrexate therapy should be carefully monitored when concomitant ciprofloxacin therapy is indicated.
Metoclopramide significantly accelerates the absorption of oral ciprofloxacin resulting in shorter time to reach maximum plasma concentrations. No significant effect was observed on the bioavailability of ciprofloxacin.
Non-steroidal anti-inflammatory drugs (but not acetyl salicylic acid) in combination of very high doses of quinolones have been shown to provoke convulsions in pre-clinical studies.

Carcinogenesis, Mutagenesis, Impairment of Fertility:

Eight in vitro mutagenicity tests have been conducted with ciprofloxacin, and the test results are listed below:
Salmonella/Microsome Test (Negative)
E. coli DNA Repair Assay (Negative)
Mouse Lymphoma Cell Forward Mutation Assay (Positive)
Chinese Hamster V79 Cell HGPRT Test (Negative)
Syrian Hamster Embryo Cell Transformation Assay (Negative)
Saccharomyces cerevisiae Point Mutation Assay (Negative)
Saccharomyces cerevisiae Mitotic Crossover and Gene Conversion Assay (Negative)
Rat Hepatocyte DNA Repair Assay (Positive)
Thus, 2 of the 8 tests were positive, but results of the following 3 in vivo test systems gave negative results:
Rat Hepatocyte DNA Repair Assay
Micronucleus Test (Mice)
Dominant Lethal Test (Mice)
Long-term carcinogenicity studies in rats and mice resulted in no carcinogenic or tumorigenic effects due to ciprofloxacin at daily oral dose levels up to 250 /kg to rats and mice, respectively (approximately 1.7- and 2.5-times the highest recommended therapeutic dose based upon mg/m^2).
Results from photo co-carcinogenicity testing indicate that ciprofloxacin does not reduce the time to appearance of UV-induced skin tumors as compared to vehicle control. Hairless (Skh-1) mice were exposed to UVA light for 3.5 hours five times every two weeks for up to 78 weeks while concurrently being administered ciprofloxacin. The time to development of the first skin tumors was 50 weeks in mice treated concomitantly with UVA and ciprofloxacin (mouse dose approximately equal to maximum recommended human dose based upon mg/m^2), as opposed to 34 weeks when animals were treated with both UVA and vehicle. The times to development of skin tumors ranged from 16-32 weeks in mice treated concomitantly with UVA and other quinolones.^4
In this model, mice treated with ciprofloxacin alone did not develop skin or systemic tumors. There are no data from similar models using pigmented mice and/or fully haired mice. The clinical significance of these findings to humans is unknown.
Fertility studies performed in rats at oral doses of ciprofloxacin up to 100 mg/kg (approximately 0.7-times the highest recommended therapeutic dose based upon mg/m^2) revealed no evidence of impairment.

Pregnancy

Teratogenic Effects

Pregnancy Category C:
There are no adequate and well-controlled studies in pregnant women. An expert review of published data on experiences with ciprofloxacin use during pregnancy by TERIS - the Teratogen Information System - concluded that therapeutic doses during pregnancy are unlikely to pose a substantial teratogenic risk (quantity and quality of data=fair), but the data are insufficient to state that there is no risk.^8
A controlled prospective observational study followed 200 women exposed to fluoroquinolones (52.5% exposed to ciprofloxacin and 68% first trimester exposures) during gestation.^9 In utero exposure to fluoroquinolones during embryogenesis was not associated with increased risk of major malformations. The reported rates of major congenital malformations were 2.2% for the fluoroquinolone group and 2.6% for the control group (background incidence of major malformations is 1-5%). Rates of spontaneous abortions, prematurity and low birth weight did not differ between the groups and there were no clinically significant musculoskeletal dysfunctions up to one year of age in the ciprofloxacin exposed children.
Another prospective follow-up study reported on 549 pregnancies with fluoroquinolone exposure (93% first trimester exposures).^10 There were 70 ciprofloxacin exposures, all within the first trimester. The malformation rates among live-born babies exposed to ciprofloxacin and to fluoroquinolones overall were both within background incidence ranges. No specific patterns of congenital abnormalities were found. The study did not reveal any clear adverse reactions due to in utero exposure to ciprofloxacin.
No differences in the rates of prematurity, spontaneous abortions, or birth weight were seen in women exposed to ciprofloxacin during pregnancy.^8,9 However, these small post-marketing epidemiology studies, of which most experience is from short term, first trimester exposure, are insufficient to evaluate the risk for less common defects or to permit reliable and definitive conclusions regarding the safety of ciprofloxacin in pregnant women and their developing fetuses. Ciprofloxacin should not be used during pregnancy unless the potential benefit justifies the potential risk to both fetus and mother (see WARNINGS).
Reproduction studies have been performed in rats and mice using oral doses up to 100 mg/kg (0.6 and 0.3 times the maximum daily human dose based upon body surface area, respectively) and have revealed no evidence of harm to the fetus due to ciprofloxacin. In rabbits, oral ciprofloxacin dose levels of 30 and 100 mg/kg (approximately 0.4- and 1.3-times the highest recommended therapeutic dose based upon mg/m^2) produced gastrointestinal toxicity resulting in maternal weight loss and an increased incidence of abortion, but no teratogenicity was observed at either dose level. After intravenous administration of doses up to 20 mg/kg (approximately 0.3-times the highest recommended therapeutic dose based upon mg/m^2) no maternal toxicity was produced and no embryotoxicity or teratogenicity was observed. (See WARNINGS.)

Nursing Mothers:

Ciprofloxacin is excreted in human milk. The amount of ciprofloxacin absorbed by the nursing infant is unknown. Because of the potential for serious adverse reactions in infants nursing from mothers taking ciprofloxacin, a decision should be made whether to discontinue nursing or to discontinue the drug, taking into account the importance of the drug to the mother.

Pediatric Use:

Ciprofloxacin, like other quinolones, causes arthropathy and histological changes in weight-bearing joints of juvenile animals resulting in lameness. (See ANIMAL PHARMACOLOGY.)

Inhalational Anthrax (Post-Exposure)

Ciprofloxacin is indicated in pediatric patients for inhalational anthrax (post-exposure). The risk-benefit assessment indicates that administration of ciprofloxacin to pediatric patients is appropriate. For information regarding pediatric dosing in inhalational anthrax (post-exposure), see Error! Hyperlink reference not valid. and INHALATIONAL ANTHRAX – ADDITIONAL INFORMATION.

Complicated Urinary Tract Infection and Pyelonephritis

Ciprofloxacin is indicated for the treatment of complicated urinary tract infections and pyelonephritis due to Escherichia coli. Although effective in clinical trials, ciprofloxacin is not a drug of first choice in the pediatric population due to an increased incidence of adverse events compared to the controls, including events related to joints and/or surrounding tissues. The rates of these events in pediatric patients with complicated urinary tract infection and pyelonephritis within six weeks of follow-up were 9.3% (31/335) versus 6% (21/349) for control agents. The rates of these events occurring at any time up to the one year follow-up were 13.7% (46/335) and 9.5% (33/349), respectively. The rate of all adverse events regardless of drug relationship at six weeks was 41% (138/335) in the ciprofloxacin arm compared to 31% (109/349) in the control arm. (See ADVERSE REACTIONS and CLINICAL STUDIES.)

Cystic Fibrosis

Short-term safety data from a single trial in pediatric cystic fibrosis patients are available. In a randomized, double-blind clinical trial for the treatment of acute pulmonary exacerbations in cystic fibrosis patients (ages 5-17 years), 67 patients received ciprofloxacin I.V. 10 mg/kg/dose q8h for one week followed by ciprofloxacin tablets 20 mg/kg/dose q12h to complete 10-21 days treatment and 62 patients received the combination of ceftazidime I.V. 50 mg/kg/dose q8h and tobramycin I.V. 3 mg/kg/dose q8h for a total of 10-21 days. Patients less than 5 years of age were not studied. Safety monitoring in the study included periodic range of motion examinations and gait assessments by treatment-blinded examiners. Patients were followed for an average of 23 days after completing treatment (range 0-93 days). This study was not designed to determine long term effects and the safety of repeated exposure to ciprofloxacin. Musculoskeletal adverse events in patients with cystic fibrosis were reported in 22% of the patients in the ciprofloxacin group and 21% in the comparison group. Decreased range of motion was reported in 12% of the subjects in the ciprofloxacin group and 16% in the comparison group. Arthralgia was reported in 10% of the patients in the ciprofloxacin group and 11% in the comparison group. Other adverse events were similar in nature and frequency between treatment arms. One of sixty-seven patients developed arthritis of the knee nine days after a ten day course of treatment with ciprofloxacin. Clinical symptoms resolved, but an MRI showed knee effusion without other abnormalities eight months after treatment. However, the relationship of this event to the patient’s course of ciprofloxacin can not be definitively determined, particularly since patients with cystic fibrosis may develop arthralgias/arthritis as part of their underlying disease process.

Geriatric Use:

Geriatric patients are at increased risk for developing severe tendon disorders including tendon rupture when being treated with a fluoroquinolone such as Ciprofloxacin Tablets USP, 250 mg and 500 mg. This risk is further increased in patients receiving concomitant corticosteroid therapy. Tendinitis or tendon rupture can involve the Achilles, hand, shoulder, or other tendon sites and can occur during or after completion of therapy; cases occurring up to several months after fluoroquinolone treatment have been reported. Caution should be used when prescribing Ciprofloxacin Tablets USP, 250 mg and 500 mg to elderly patients especially those on corticosteroids. Patients should be informed of this potential side effect and advised to discontinue Ciprofloxacin Tablets USP, 250 mg and 500 mg and contact their healthcare provider if any symptoms of tendinitis or tendon rupture occur (See Error! Hyperlink reference not valid., WARNINGS, and ADVERSE REACTIONS/Post-Marketing Adverse Event Reports).
In a retrospective analysis of 23 multiple-dose controlled clinical trials of ciprofloxacin encompassing over 3500 ciprofloxacin treated patients, 25% of patients were greater than or equal to 65 years of age and 10% were greater than or equal to 75 years of age. No overall differences in safety or effectiveness were observed between these subjects and younger subjects, and other reported clinical experience has not identified differences in responses between the elderly and younger patients, but greater sensitivity of some older individuals on any drug therapy cannot be ruled out. Ciprofloxacin is known to be substantially excreted by the kidney, and the risk of adverse reactions may be greater in patients with impaired renal function. No alteration of dosage is necessary for patients greater than 65 years of age with normal renal function. However, since some older individuals experience reduced renal function by virtue of their advanced age, care should be taken in dose selection for elderly patients, and renal function monitoring may be useful in these patients. (See CLINICAL PHARMACOLOGY and Error! Hyperlink reference not valid..)
In general, elderly patients may be more susceptible to drug-associated effects on the QT interval. Therefore, precaution should be taken when using Ciprofloxacin Tablets USP 250 mg and 500 mg with concomitant drugs that can result in prolongation of the QT interval (e.g., class IA or class III antiarrhythmics) or in patients with risk factors for torsade de pointes (e.g., known QT prolongation, uncorrected hypokalemia).

ADVERSE REACTIONS

Adverse Reactions in Adult Patients:

During clinical investigations with oral and parenteral ciprofloxacin, 49,038 patients received courses of the drug. Most of the adverse events reported were described as only mild or moderate in severity, abated soon after the drug was discontinued, and required no treatment. Ciprofloxacin was discontinued because of an adverse event in 1% of orally treated patients.
The most frequently reported drug related events, from clinical trials of all formulations, all dosages, all drug-therapy durations, and for all indications of ciprofloxacin therapy were nausea (2.5%), diarrhea (1.6%), liver function tests abnormal (1.3%), vomiting (1%), and rash (1%).
Additional medically important events that occurred in less than 1% of ciprofloxacin patients are listed below.
BODY AS A WHOLE: headache, abdominal pain/discomfort, foot pain, pain, pain in extremities, injection site reaction (ciprofloxacin intravenous)
CARDIOVASCULAR: palpitation, atrial flutter, ventricular ectopy, syncope, hypertension, angina pectoris, myocardial infarction, cardiopulmonary arrest, cerebral thrombosis, phlebitis, tachycardia, migraine, hypotension
CENTRAL NERVOUS SYSTEM: restlessness, dizziness, lightheadedness, insomnia, nightmares, hallucinations, manic reaction, irritability, tremor, ataxia, convulsive seizures, lethargy, drowsiness, weakness, malaise, anorexia, phobia, depersonalization, depression, paresthesia, abnormal gait, grand mal convulsion
GASTROINTESTINAL: painful oral mucosa, oral candidiasis, dysphagia, intestinal perforation, gastrointestinal bleeding, cholestatic jaundice, hepatitis
HEMIC/LYMPHATIC: lymphadenopathy, petechia
METABOLIC/NUTRITIONAL: amylase increase, lipase increase
MUSCULOSKELETAL: arthralgia or back pain, joint stiffness, achiness, neck or chest pain, flare up of gout
RENAL/UROGENITAL: interstitial nephritis, nephritis, renal failure, polyuria, urinary retention, urethral bleeding, vaginitis, acidosis, breast pain
RESPIRATORY: dyspnea, epistaxis, laryngeal or pulmonary edema, hiccough, hemoptysis, bronchospasm, pulmonary embolism
SKIN/HYPERSENSITIVITY: allergic reaction, pruritus, urticaria, photosensitivity/phototoxicity reaction, flushing, fever, chills, angioedema, edema of the face, neck, lips, conjunctivae or hands, cutaneous candidiasis, hyperpigmentation, erythema nodosum, sweating
SPECIAL SENSES: blurred vision, disturbed vision (change in color perception, overbrightness of lights), decreased visual acuity, diplopia, eye pain, tinnitus, hearing loss, bad taste, chromatopsia
In several instances nausea, vomiting, tremor, irritability, or palpitation were judged by investigators to be related to elevated serum levels of theophylline possibly as a result of drug interaction with ciprofloxacin.
In randomized, double-blind controlled clinical trials comparing ciprofloxacin tablets (500 mg BID) to cefuroxime axetil (250 mg-500 mg BID) and to clarithromycin (500 mg BID) in patients with respiratory tract infections, ciprofloxacin demonstrated a CNS adverse event profile comparable to the control drugs.

Adverse Reactions in Pediatric Patients:

Ciprofloxacin, administered I.V. and /or orally, was compared to a cephalosporin for treatment of complicated urinary tract infections (cUTI) or pyelonephritis in pediatric patients 1 to 17 years of age (mean age of 6 ± 4 years). The trial was conducted in the US, Canada, Argentina, Peru, Costa Rica, Mexico, South Africa, and Germany. The duration of therapy was 10 to 21 days (mean duration of treatment was 11 days with a range of 1 to 88 days). The primary objective of the study was to assess musculoskeletal and neurological safety within 6 weeks of therapy and through one year of follow-up in the 335 ciprofloxacin- and 349 comparator-treated patients enrolled.
An Independent Pediatric Safety Committee (IPSC) reviewed all cases of musculoskeletal adverse events as well as all patients with an abnormal gait or abnormal joint exam (baseline or treatment-emergent). These events were evaluated in a comprehensive fashion and included such conditions as arthralgia, abnormal gait, abnormal joint exam, joint sprains, leg pain, back pain, arthrosis, bone pain, pain, myalgia, arm pain, and decreased range of motion in a joint. The affected joints included: knee, elbow, ankle, hip, wrist, and shoulder. Within 6 weeks of treatment initiation, the rates of these events were 9.3% (31/335) in the ciprofloxacin-treated group versus 6% (21/349) in comparator-treated patients. The majority of these events were mild or moderate in intensity. All musculoskeletal events occurring by 6 weeks resolved (clinical resolution of signs and symptoms), usually within 30 days of end of treatment. Radiological evaluations were not routinely used to confirm resolution of the events. The events occurred more frequently in ciprofloxacin-treated patients than control patients, regardless of whether they received I.V. or oral therapy. Ciprofloxacin-treated patients were more likely to report more than one event and on more than one occasion compared to control patients. These events occurred in all age groups and the rates were consistently higher in the ciprofloxacin group compared to the control group. At the end of 1 year, the rate of these events reported at any time during that period was 13.7% (46/335) in the ciprofloxacin-treated group versus 9.5% (33/349) comparator-treated patients.
An adolescent female discontinued ciprofloxacin for wrist pain that developed during treatment. An MRI performed 4 weeks later showed a tear in the right ulnar fibrocartilage. A diagnosis of overuse syndrome secondary to sports activity was made, but a contribution from ciprofloxacin cannot be excluded. The patient recovered by 4 months without surgical intervention.

Findings Involving Joint or Peri-articular Tissues as Assessed by the IPSC
 | Ciprofloxacin | Comparator
All Patients (within 6 weeks) | 31/335 (9.3%) | 21/349 (6%)
95% Confidence Interval* | (-0.8%, +7.2%)
Age Group
≥ 12 months < 24 months | 1/36 (2.8%) | 0/41
≥ 2 years < 6 years | 5/124 (4%) | 3/118 (2.5%)
≥ 6 years < 12 years | 18/143 (12.6%) | 12/153 (7.8%)
≥ 12 years to 17 years | 7/32 (21.9%) | 6/37 (16.2 %)
All Patients (within 1 year) | 46/335 (13.7%) | 33/349 (9.5%)
95% Confidence Interval* | (-0.6%, + 9.1%)
*The study was designed to demonstrate that the arthropathy rate for the ciprofloxacin group did not exceed
that of the control group by more than + 6%. At both the 6 week and 1 year evaluations, the 95% confidence
interval indicated that it could not be concluded that ciprofloxacin group had findings comparable to the control group.

The incidence rates of neurological events within 6 weeks of treatment initiation were 3% (9/335) in the ciprofloxacin group versus 2% (7/349) in the comparator group and included dizziness, nervousness, insomnia, and somnolence.
In this trial, the overall incidence rates of adverse events regardless of relationship to study drug and within 6 weeks of treatment initiation were 41% (138/335) in the ciprofloxacin group versus 31% (109/349) in the comparator group. The most frequent events were gastrointestinal: 15% (50/335) of ciprofloxacin patients compared to 9% (31/349) of comparator patients. Serious adverse events were seen in 7.5% (25/335) of ciprofloxacin-treated patients compared to 5.7% (20/349) of control patients. Discontinuation of drug due to an adverse event was observed in 3% (10/335) of ciprofloxacin-treated patients versus 1.4% (5/349) of comparator patients. Other adverse events that occurred in at least 1% of ciprofloxacin patients were diarrhea 4.8%, vomiting 4.8%, abdominal pain 3.3%, accidental injury 3%, rhinitis 3%, dyspepsia 2.7%, nausea 2.7%, fever 2.1%, asthma 1.8% and rash 1.8%.
In addition to the events reported in pediatric patients in clinical trials, it should be expected that events reported in adults during clinical trials or post-marketing experience may also occur in pediatric patients.

Post-Marketing Adverse Event Reports:

The following adverse events have been reported from worldwide marketing experience with quinolones, including ciprofloxacin. Because these events are reported voluntarily from a population of uncertain size, it is not always possible to reliably estimate their frequency or establish a causal relationship to drug exposure. Decisions to include these events in labeling are typically based on one or more of the following factors: (1) seriousness of the event, (2) frequency of the reporting, or (3) strength of causal connection to the drug.
Agitation, agranulocytosis, albuminuria, anaphylactic reactions (including life-threatening anaphylactic shock), anosmia, candiduria, cholesterol elevation (serum), confusion, constipation, delirium, dyspepsia, dysphagia, erythema multiforme, exfoliative dermatitis, fixed eruption, flatulence, glucose elevation (blood), hemolytic anemia, hepatic failure (including fatal cases), hepatic necrosis, hyperesthesia, hypertonia, hypesthesia, hypotension (postural), jaundice, marrow depression (life threatening), methemoglobinemia, moniliasis (oral, gastrointestinal, vaginal), myalgia, myasthenia, myasthenia gravis (possible exacerbation), myoclonus, nystagmus, pancreatitis, pancytopenia (life threatening or fatal outcome), peripheral neuropathy, phenytoin alteration (serum), photosensitivity/phototoxicity reaction, potassium elevation (serum), prothrombin time prolongation or decrease, pseudomembranous colitis (The onset of pseudomembranous colitis symptoms may occur during or after antimicrobial treatment.), psychosis (toxic), renal calculi, serum sickness like reaction, Stevens-Johnson syndrome, taste loss, tendinitis, tendon rupture, torsade de pointes, toxic epidermal necrolysis (Lyell’s Syndrome), triglyceride elevation (serum), twitching, vaginal candidiasis, and vasculitis. (See PRECAUTIONS.)
Adverse events were also reported by persons who received ciprofloxacin for anthrax post-exposure prophylaxis following the anthrax bioterror attacks of October 2001. (See also INHALATIONAL ANTHRAX – ADDITIONAL INFORMATION.)

Adverse Laboratory Changes:

Changes in laboratory parameters listed as adverse events without regard to drug relationship are listed below:
Hepatic – Elevations of ALT (SGPT) (1.9%), AST (SGOT) (1.7%), alkaline phosphatase (0.8%), LDH (0.4%), serum bilirubin (0.3%).
Hematologic – Eosinophilia (0.6%), leukopenia (0.4%), decreased blood platelets (0.1%), elevated blood platelets (0.1%), pancytopenia (0.1%).
Renal – Elevations of serum creatinine (1.1%), BUN (0.9%), CRYSTALLURIA, CYLINDRURIA, AND HEMATURIA HAVE BEEN REPORTED.
Other changes occurring in less than 0.1% of courses were: elevation of serum gammaglutamyl transferase, elevation of serum amylase, reduction in blood glucose, elevated uric acid, decrease in hemoglobin, anemia, bleeding diathesis, increase in blood monocytes, leukocytosis.

OVERDOSAGE

In the event of acute overdosage, reversible renal toxicity has been reported in some cases. The stomach should be emptied by inducing vomiting or by gastric lavage. The patient should be carefully observed and given supportive treatment, including monitoring of renal function and administration of magnesium, aluminum, or calcium containing antacids which can reduce the absorption of ciprofloxacin. Adequate hydration must be maintained. Only a small amount of ciprofloxacin (< 10%) is removed from the body after hemodialysis or peritoneal dialysis.
Single doses of ciprofloxacin were relatively non-toxic via the oral route of administration in mice, rats, and dogs. No deaths occurred within a 14-day post treatment observation period at the highest oral doses tested; up to 5000 mg/kg in either rodent species, or up to 2500 mg/kg in the dog. Clinical signs observed included hypoactivity and cyanosis in both rodent species and severe vomiting in dogs. In rabbits, significant mortality was seen at doses of ciprofloxacin > 2500 mg/kg. Mortality was delayed in these animals, occurring 10-14 days after dosing.
In mice, rats, rabbits and dogs, significant toxicity including tonic/clonic convulsions was observed at intravenous doses of ciprofloxacin between 125 and 300 mg/kg.

DOSAGE AND ADMINISTRATION

DOSAGE AND ADMINISTRATION - ADULTS

Ciprofloxacin Tablets USP 250 mg and 500 mg should be administered orally to adults as described in the Dosage Guidelines table.
The determination of dosage for any particular patient must take into consideration the severity and nature of the infection, the susceptibility of the causative organism, the integrity of the patient’s host-defense mechanisms, and the status of renal function and hepatic function.
The duration of treatment depends upon the severity of infection. The usual duration is 7 to 14 days; however, for severe and complicated infections more prolonged therapy may be required. Ciprofloxacin should be administered at least 2 hours before or 6 hours after magnesium/aluminum antacids, or sucralfate, Videx® (didanosine) chewable/buffered tablets or pediatric powder for oral solution, other highly buffered drugs, or other products containing calcium, iron or zinc.

ADULT DOSAGE GUIDELINES
Infection | Severity | Dose | Frequency | Usual Durations†
Urinary Tract | Acute Uncomplicated | 250 mg | q 12 h | 3 Days
Urinary Tract | Mild/Moderate | 250 mg | q 12 h | 7 to 14 Days
Urinary Tract | Severe/Complicated | 500 mg | q 12 h | 7 to 14 Days
Chronic Bacterial Prostatits | Mild/Moderate | 500 mg | q 12 h | 28 Days
Lower Respiratory Tract | Mild/Moderate | 500 mg | q 12 h | 7 to 14 days
Lower Respiratory Tract | Severe/Complicated | 750 mg | q 12 h | 7 to 14 days
Acute Sinusitis | Mild/Moderate | 500 mg | q 12 h | 10 days
Skin and Skin Structure | Mild/Moderate | 500 mg | q 12 h | 7 to 14 Days
Skin and Skin Structure | Severe/Complicated | 750 mg | q 12 h | 7 to 14 Days
Bone and Joint | Mild/Moderate | 500 mg | q 12 h | ≥4 to 6 weeks
Bone and Joint | Severe/Complicated | 750 mg | q 12 h | ≥4 to 6 weeks
Intra-Abdominal* | Complicated | 500 mg | q 12 h | 7 to 14 Days
Infectious Diarrhea | Mild/Moderate/Severe | 500 mg | q 12 h | 5 to 7 Days
Typhoid Fever | Mild/Moderate | 500 mg | q 12 h | 10 Days
Urethral and Cervical Gonococcal Infections | Uncomplicated | 250 mg | single dose | single dose
Inhalational anthrax (post-exposure)** |  | 500 mg | q 12 h | 60 Days
* used in conjunction with metronidazole
† Generally ciprofloxacin should be continued for at least 2 days after the signs and symptoms of infection
have disappeared, except for inhalational anthrax (post-exposure).
** Drug administration should begin as soon as possible after suspected or confirmed exposure.
This indication is based on a surrogate endpoint, ciprofloxacin serum concentrations achieved in humans,
reasonably likely to predict clinical benefit.^4 For a discussion of ciprofloxacin serum concentrations in various
human populations, see INHALATIONAL ANTHRAX – ADDITIONAL INFORMATION.

Conversion of I.V. to Oral Dosing in Adults:
Patients whose therapy is started with CIPRO I.V. may be switched to Ciprofloxacin Tablets USP 250 mg and 500 mg when clinically indicated at the discretion of the physician (See CLINICAL PHARMACOLOGY and table below for the equivalent dosing regimens).

Equivalent AUC Dosing Regimens
Cipro Oral Dosage | Equivalent Cipro I.V. Dosage
250 mg Tablet q 12 h | 200 mg I.V. q 12 h
500 mg Tablet q 12 h | 400 mg I.V. q 12 h
750 mg Tablet q 12 h | 400 mg I.V. q 8 h

Adults with Impaired Renal Function:
Ciprofloxacin is eliminated primarily by renal excretion; however, the drug is also metabolized and partially cleared through the biliary system of the liver and through the intestine. These alternative pathways of drug elimination appear to compensate for the reduced renal excretion in patients with renal impairment. Nonetheless, some modification of dosage is recommended, particularly for patients with severe renal dysfunction. The following table provides dosage guidelines for use in patients with renal impairment:

RECOMMENDED STARTING AND MAINTENANCE DOSES FOR PATIENTS WITH IMPAIRED RENAL FUNCTION
Creatinine Clearance (mL/min) | Dose
> 50 | See Usual Dosage.
30-50 | 250-500 mg q 12 h
5-29 | 250-500 mg q 18 h
Patients on hemodialysis or Peritoneal dialysis | 250-500 mg q 24 h (after dialysis)

When only the serum creatinine concentration is known, the following formula may be used to estimate creatinine clearance.
Weight (kg) x (140 - age)
Men: Creatinine clearance (mL/min) = 72 x serum creatinine (mg/dL)
Women: 0.85 x the value calculated for men.
The serum creatinine should represent a steady state of renal function.
In patients with severe infections and severe renal impairment, a unit dose of 750 mg may be administered at the intervals noted above. Patients should be carefully monitored.

DOSAGE AND ADMINISTRATION - PEDIATRICS

Ciprofloxacin Tablets USP 250 mg and 500 mg should be administered orally as described in the Dosage Guidelines table. An increased incidence of adverse events compared to controls, including events related to joints and/or surrounding tissues, has been observed. (See ADVERSE REACTIONS and CLINICAL STUDIES.)
Dosing and initial route of therapy (i.e., I.V. or oral) for complicated urinary tract infection or pyelonephritis should be determined by the severity of the infection. In the clinical trial, pediatric patients with moderate to severe infection were initiated on 6 to 10 mg/kg I.V. every 8 hours and allowed to switch to oral therapy (10 to 20 mg/kg every 12 hours), at the discretion of the physician.

PEDIATRIC DOSAGE GUIDELINES
Infection | Route of Administration | Dose (mg/kg) | Frequency | Total Duration
Complicated Urinary Tract or Pyelonephritis | Intravenous | 6 to 10 mg/kg (maximum 400 mg per dose; not to be exceeded even in patients weighing > 51 kg) | Every 8 hours | 10-21 days*
(patients from 1 to 17 years of age) | Oral | 10 mg/kg to 20 mg/kg (maximum 750 mg per dose; not to be exceeded even in patients weighing > 51 kg) | Every 12 hours | 10-21 days*
Inhalational Anthrax (Post-Exposure)** | Intravenous | 10 mg/kg (maximum 400 mg per dose) | Every 12 hours | 60 days
Inhalational Anthrax (Post-Exposure)** | Oral | 15 mg/kg (maximum 500 mg per dose) | Every 12 hours | 60 days
* The total duration of therapy for complicated urinary tract infection and pyelonephritis in
the clinical trial was determined by the physician. The mean duration of treatment was
11 days (range 10 to 21 days).
** Drug administration should begin as soon as possible after suspected or confirmed
exposure to Bacillus anthracis spores. This indication is based on a surrogate endpoint,
ciprofloxacin serum concentrations achieved in humans, reasonably likely to predict
clinical benefit.^5 For a discussion of ciprofloxacin serum concentrations in various
human populations, see INHALATIONAL ANTHRAX – ADDITIONAL INFORMATION.

Pediatric patients with moderate to severe renal insufficiency were excluded from the clinical trial of complicated urinary tract infection and pyelonephritis. No information is available on dosing adjustments necessary for pediatric patients with moderate to severe renal insufficiency (i.e., creatinine clearance of < 50 mL/min/1.73m^2).

HOW SUPPLIED

Ciprofloxacin tablets USP 250 mg are available as white colored, biconvex, circular, film coated tablets, debossed ‘P’ on one side and ‘250’ on the other side containing ciprofloxacin hydrochloride, USP equivalent to 250 mg of ciprofloxacin. Ciprofloxacin tablets USP 500 mg tablet are available as white colored, biconvex, capsule shaped, film coated tablets, debossed ‘P’ on one side and ‘500’ on the other side containing ciprofloxacin hydrochloride, USP equivalent to 500 mg ciprofloxacin.

 | Strength | NDC Code | Tablet Identification
Bottles of 6:; Bottles of 10:; Bottles of 14:; Bottles of 20:; Bottles of 28:; Bottles of 30:; Bottles of 60:; Bottles of 90:; Bottles of 06:; Bottles of 10:; Bottles of 14:; Bottles of 20:; Bottles of 28:; Bottles of 30:; Bottles of 60:; Bottles of 90: | 250 mg; 250 mg; 250 mg; 250 mg; 250 mg; 250 mg; 250 mg; 250 mg; 500 mg; 500 mg; 500 mg; 500 mg 500 mg; 500 mg; 500 mg; 500 mg | NDC 63187-142-06; NDC 63187-142-10; NDC 63187-142-14; NDC 63187-142-20; NDC 63187-142-28; NDC 63187-142-30; NDC 63187-142-60; NDC 63187-142-90; NDC 63187-017-06; NDC 63187-017-10; NDC 63187-017-14; NDC 63187-017-20 NDC 63187-017-28; NDC 63187-017-30; NDC 63187-017-60; NDC 63187-017-90 | P 250; P 250; P 250; P 250; P 250; P 250; P 250; P 250; P 500; P 500; P 500; P 500; P 500; P 500; P 500; P 500

Store at 20° to 25°C (68° to 77°F)

Manufactured by:
Unique Pharmaceutical Laboratories
(A Div. of J.B. Chemicals & Pharmaceuticals Ltd.),
Mumbai 400 030, India

Distributed by:
Rising Pharmaceuticals, Inc.
Saddle Brook, NJ 07663

Repackaged by:
Proficient Rx LP
Thousand Oaks, CA 91320

ANIMAL PHARMACOLOGY

Ciprofloxacin and other quinolones have been shown to cause arthropathy in immature animals of most species tested. (See WARNINGS.) Damage of weight bearing joints was observed in juvenile dogs and rats. In young beagles, 100 mg/kg ciprofloxacin, given daily for 4 weeks, caused degenerative articular changes of the knee joint. At 30 mg/kg, the effect on the joint was minimal. In a subsequent study in young beagle dogs, oral ciprofloxacin doses of 30 mg/kg and 90 mg/kg ciprofloxacin (approximately 1.3- and 3.5-times the pediatric dose based upon comparative plasma AUCs) given daily for 2 weeks caused articular changes which were still observed by histopathology after a treatment-free period of 5 months. At 10 mg/kg (approximately 0.6-times the pediatric dose based upon comparative plasma AUCs), no effects on joints were observed. This dose was also not associated with arthrotoxicity after an additional treatment-free period of 5 months. In another study, removal of weight bearing from the joint reduced the lesions but did not totally prevent them.
Crystalluria, sometimes associated with secondary nephropathy, occurs in laboratory animals dosed with ciprofloxacin. This is primarily related to the reduced solubility of ciprofloxacin under alkaline conditions, which predominate in the urine of test animals; in man, crystalluria is rare since human urine is typically acidic. In rhesus monkeys, crystalluria without nephropathy was noted after single oral doses as low as 5 mg/kg. (approximately 0.07-times the highest recommended therapeutic dose based upon mg/m^2). After 6 months of intravenous dosing at 10 mg/kg/day, no nephropathological changes were noted; however, nephropathy was observed after dosing at 20 mg/kg/day for the same duration (approximately 0.2-times the highest recommended therapeutic dose based upon mg/m^2).
In dogs, ciprofloxacin at 3 and 10 mg/kg by rapid I.V. injection (15 sec.) produces pronounced hypotensive effects. These effects are considered to be related to histamine release, since they are partially antagonized by pyrilamine, an antihistamine. In rhesus monkeys, rapid I.V. injection also produces hypotension but the effect in this species is inconsistent and less pronounced.
In mice, concomitant administration of nonsteroidal anti-inflammatory drugs such as phenylbutazone and indomethacin with quinolones has been reported to enhance the CNS stimulatory effect of quinolones.
Ocular toxicity seen with some related drugs has not been observed in ciprofloxacin-treated animals.

CLINICAL STUDIES

Complicated Urinary Tract Infection and Pyelonephritis – Efficacy in Pediatric Patients:

NOTE: Although effective in clinical trials, ciprofloxacin is not a drug of first choice in the pediatric population due to an increased incidence of adverse events compared to controls, including events related to joints and/or surrounding tissues.
Ciprofloxacin, administered I.V. and/or orally, was compared to a cephalosporin for treatment of complicated urinary tract infections (cUTI) and pyelonephritis in pediatric patients 1 to 17 years of age (mean age of 6 ± 4 years). The trial was conducted in the US, Canada, Argentina, Peru, Costa Rica, Mexico, South Africa, and Germany. The duration of therapy was 10 to 21 days (mean duration of treatment was 11 days with a range of 1 to 88 days). The primary objective of the study was to assess musculoskeletal and neurological safety.
Patients were evaluated for clinical success and bacteriological eradication of the baseline organism(s) with no new infection or superinfection at 5 to 9 days post-therapy (Test of Cure or TOC). The Per Protocol population had a causative organism(s) with protocol specified colony count(s) at baseline, no protocol violation, and no premature discontinuation or loss to follow-up (among other criteria).
The clinical success and bacteriologic eradication rates in the Per Protocol population were similar between ciprofloxacin and the comparator group as shown below.

Clinical Success and Bacteriologic Eradication at Test of Cure (5 to 9 Days Post-Therapy)
 | Ciprofloxacin | Comparator
Randomized Patients | 337 | 352
Per Protocol Patients | 211 | 231
Clinical Response at 5 to 9 Days Post-Treatment | 95.7% (202/211) | 92.6% (214/231)
 | 95% CI [-1.3%, 7.3%]
Bacteriologic Eradication by Patient at 5 to 9 Days Post-Treatment* | 84.4% (178/211) | 78.3% (181/231)
 | 95% CI [-1.3%, 13.1%]
Bacteriologic Eradication of the Baseline Pathogen at 5 to 9 Days Post-Treatment
Escherichia coli | 156/178 (88%) | 161/179 (90%)
* Patients with baseline pathogen(s) eradicated and no new infections or
superinfections/total number of patients. There were 5.5% (6/211) ciprofloxacin and
9.5% (22/231) comparator patients with superinfections or new infections.

INHALATIONAL ANTHRAX IN ADULTS AND PEDIATRICS – ADDITIONAL INFORMATION

The mean serum concentrations of ciprofloxacin associated with a statistically significant improvement in survival in the rhesus monkey model of inhalational anthrax are reached or exceeded in adult and pediatric patients receiving oral and intravenous regimens. (See Error! Hyperlink reference not valid..) Ciprofloxacin pharmacokinetics have been evaluated in various human populations. The mean peak serum concentration achieved at steady-state in human adults receiving 500 mg orally every 12 hours is 2.97 μg/mL, and 4.56 μg/mL following 400 mg intravenously every 12 hours. The mean trough serum concentration at steady-state for both of these regimens is 0.2 μg/mL. In a study of 10 pediatric patients between 6 and 16 years of age, the mean peak plasma concentration achieved is 8.3 μg/mL and trough concentrations range from 0.09 to 0.26 μg/mL, following two 30-minute intravenous infusions of 10 mg/kg administered 12 hours apart. After the second intravenous infusion patients switched to 15 mg/kg orally every 12 hours achieve a mean peak concentration of 3.6 μg/mL after the initial oral dose. Long-term safety data, including effects on cartilage, following the administration of ciprofloxacin to pediatric patients are limited. (For additional information, see PRECAUTIONS, Pediatric Use.) Ciprofloxacin serum concentrations achieved in humans serve as a surrogate endpoint reasonably likely to predict clinical benefit and provide the basis for this indication.^5
A placebo-controlled animal study in rhesus monkeys exposed to an inhaled mean dose of 11 LD50 (~5.5 x 10^5 spores (range 5-30 LD50) of B. anthracis was conducted. The minimal inhibitory concentration (MIC) of ciprofloxacin for the anthrax strain used in this study was 0.08 μg/mL. In the animals studied, mean serum concentrations of ciprofloxacin achieved at expected Tmax (1 hour post-dose) following oral dosing to steady-state ranged from 0.98 to 1.69 μg/mL. Mean steady-state trough concentrations at 12 hours post-dose ranged from 0.12 to 0.19 μg/mL.^6 Mortality due to anthrax for animals that received a 30-day regimen of oral ciprofloxacin beginning 24 hours post-exposure was significantly lower (1/9), compared to the placebo group (9/10) [p=0.001]. The one ciprofloxacin-treated animal that died of anthrax did so following the 30-day drug administration period.^7
More than 9300 persons were recommended to complete a minimum of 60 days of antibiotic prophylaxis against possible inhalational exposure to B. anthracis during 2001. Ciprofloxacin was recommended to most of those individuals for all or part of the prophylaxis regimen. Some persons were also given anthrax vaccine or were switched to alternative antibiotics. No one who received ciprofloxacin or other therapies as prophylactic treatment subsequently developed inhalational anthrax. The number of persons who received ciprofloxacin as all or part of their post-exposure prophylaxis regimen is unknown.
Among the persons surveyed by the Centers for Disease Control and Prevention, over 1000 reported receiving ciprofloxacin as sole post-exposure prophylaxis for inhalational anthrax. Gastrointestinal adverse events (nausea, vomiting, diarrhea, or stomach pain), neurological adverse events (problems sleeping, nightmares, headache, dizziness or lightheadedness) and musculoskeletal adverse events (muscle or tendon pain and joint swelling or pain) were more frequent than had been previously reported in controlled clinical trials. This higher incidence, in the absence of a control group, could be explained by a reporting bias, concurrent medical conditions, other concomitant medications, emotional stress or other confounding factors, and/or a longer treatment period with ciprofloxacin. Because of these factors and limitations in the data collection, it is difficult to evaluate whether the reported symptoms were drug-related.

REFERENCES:

- National Committee for Clinical Laboratory Standards, Methods for Dilution Antimicrobial Susceptibility Tests for Bacteria That Grow Aerobically-Fifth Edition. Approved Standard NCCLS Document M7-A5, Vol. 20, No. 2, NCCLS, Wayne, PA, January, 2000.
- Clinical and Laboratory Standards Institute, Methods for Antimicrobial Dilution and Disk Susceptibility Testing of Infrequently Isolated or Fastidious Bacteria; Approved Guideline., CLSI Document M45-A, Vol. 26, No. 19, CLSI, Wayne, PA, 2006.
- National Committee for Clinical Laboratory Standards, Performance Standards for Antimicrobial Disk Susceptibility Tests-Seventh Edition. Approved Standard NCCLS Document M2-A7, Vol. 20, No. 1, NCCLS, Wayne, PA, January, 2000.
- Report presented at the FDA’s Anti-Infective Drug and Dermatological Drug Product’s Advisory Committee meeting, March 31, 1993, Silver Spring, MD. Report available from FDA, CDER, Advisors and Consultants Staff, HFD-21, 1901 Chapman Avenue, Room 200, Rockville, MD 20852, USA.
- 21 CFR 314.510 (Subpart H – Accelerated Approval of New Drugs for Life-Threatening Illnesses).
- Kelly DJ, et al. Serum concentrations of penicillin, doxycycline, and ciprofloxacin during prolonged therapy in rhesus monkeys. J Infect Dis 1992; 166:1184-7.
- Friedlander AM, et al. Postexposure prophylaxis against experimental inhalational anthrax. J Infect Dis 1993; 167:1239-42.
- Friedman J, Polifka J. Teratogenic effects of drugs: a resource for clinicians (TERIS). Baltimore, Maryland: Johns Hopkins University Press, 2000:149-195.
- Loebstein R, Addis A, Ho E, et al. Pregnancy outcome following gestational exposure to fluoroquinolones: a multicenter prospective controlled study. Antimicrob Agents Chemother. 1998;42(6):1336-1339.
- Schaefer C, Amoura-Elefant E, Vial T, et al. Pregnancy outcome after prenatal quinolone exposure. Evaluation of a case registry of the European network of teratology information services (ENTIS). Eur J Obstet Gynecol Reprod Biol. 1996;69:83-89.

Ciprofloxacin Tablets USP, 250 mg and 500 mg

Read the Medication Guide that comes with Ciprofloxacin Tablets USP before you start taking it and each time you get a refill. There may be new information. This Medication Guide does not take the place of talking to your healthcare provider about your medical condition or your treatment.

What is the most important information I should know about Ciprofloxacin Tablets USP ?

Ciprofloxacin Tablets USP belongs to a class of antibiotics called fluoroquinolones. Ciprofloxacin Tablets USP can cause side effects that may be serious or even cause death. If you get any of the following serious side effects, get medical help right away. Talk with your healthcare provider about whether you should continue to take Ciprofloxacin Tablets USP.

Tendon rupture or swelling of the tendon (tendinitis)

- Tendons are tough cords of tissue that connect muscles to bones.
- Pain, swelling, tears and inflammation of tendons including the back of the ankle (Achilles), shoulder, hand, or other tendon sites can happen in people of all ages who take fluoroquinolone antibiotics, including Ciprofloxacin Tablets USP. The risk of getting tendon problems is higher if you:
  - are over 60 years of age
  - are taking steroids (corticosteroids)
  - have had a kidney, heart or lung transplant
- Swelling of the tendon (tendinitis) and tendon rupture (breakage) have also happened in patients who take fluoroquinolones who do not have the above risk factors.
- Other reasons for tendon ruptures can include:
  - physical activity or exercise
  - kidney failure
  - tendon problems in the past, such as in people with rheumatoid arthritis (RA)
- Call your healthcare provider right away at the first sign of tendon pain, swelling or inflammation. Stop taking Ciprofloxacin Tablets USP until tendinitis or tendon rupture has been ruled out by your healthcare provider. Avoid exercise and using the affected area. The most common area of pain and swelling is the Achilles tendon at the back of your ankle. This can also happen with other tendons. Talk to your healthcare provider about the risk of tendon rupture with continued use of Ciprofloxacin Tablets USP. You may need a different antibiotic that is not a fluoroquinolone to treat your infection.
- Tendon rupture can happen while you are taking or after you have finished taking Ciprofloxacin Tablets USP. Tendon ruptures have happened up to several months after patients have finished taking their fluoroquinolone.
- Get medical help right away if you get any of the following signs or symptoms of a tendon rupture:
  - hear or feel a snap or pop in a tendon area
  - bruising right after an injury in a tendon area
  - unable to move the affected area or bear weight
- See the section “What are the possible side effects of Ciprofloxacin Tablets USP?” for more information about side effects.

What is Ciprofloxacin Tablets USP?

Ciprofloxacin Tablets USP is a fluoroquinolone antibiotic medicine used to treat certain infections caused by certain germs called bacteria.

Children less than 18 years of age have a higher chance of getting bone, joint, or tendon (musculoskeletal) problems such as pain or swelling while taking Ciprofloxacin Tablets USP. Ciprofloxacin Tablets USP should not be used as the first choice of antibiotic medicine in children under 18 years of age.

Ciprofloxacin Tablets USP should not be used in children under 18 years old, except to treat specific serious infections, such as complicated urinary tract infections and to prevent anthrax disease after breathing the anthrax bacteria germ (inhalational exposure). It is not known if Ciprofloxacin Extended Release Tablets are safe and work in children under 18 years of age.

Sometimes infections are caused by viruses rather than by bacteria. Examples include viral infections in the sinuses and lungs, such as the common cold or flu. Antibiotics, including Ciprofloxacin Tablets USP, do not kill viruses.

Call your healthcare provider if you think your condition is not getting better while you are taking Ciprofloxacin Tablets USP.

Who should not take Ciprofloxacin Tablets USP?

Do not take Ciprofloxacin Tablets USP if you:

- have ever had a severe allergic reaction to an antibiotic known as a fluoroquinolone, or are allergic to any of the ingredients in Ciprofloxacin Tablets USP. Ask your healthcare provider if you are not sure. See the list of ingredients in Ciprofloxacin Tablets USP at the end of this Medication Guide.
- also take a medicine called tizanidine (Zanaflex®). Serious side effects from tizanidine are likely to happen.

What should I tell my healthcare provider before taking Ciprofloxacin Tablets USP?

See “What is the most important information I should know about Ciprofloxacin Tablets USP?”

Tell your healthcare provider about all your medical conditions, including if you:

- have tendon problems
- have central nervous system problems (such as epilepsy)
- have nerve problems
- have or anyone in your family has an irregular heartbeat, especially a condition called “QT prolongation”
- have a history of seizures
- have kidney problems. You may need a lower dose of Ciprofloxacin Tablets USP if your kidneys do not work well.
- have rheumatoid arthritis (RA) or other history of joint problems
- have trouble swallowing pills
- are pregnant or planning to become pregnant. It is not known if Ciprofloxacin Tablets USP will harm your unborn child.
- are breast-feeding or planning to breast-feed. Ciprofloxacin Tablets USP passes into breast milk. You and your healthcare provider should decide whether you will take Ciprofloxacin Tablets USP or breast-feed.

Tell your healthcare provider about all the medicines you take, including prescription and non-prescription medicines, vitamins and herbal and dietary supplements. Ciprofloxacin Tablets USP and other medicines can affect each other causing side effects. Especially tell your healthcare provider if you take:

- an NSAID (Non-Steroidal Anti-Inflammatory Drug). Many common medicines for pain relief are NSAIDs. Taking an NSAID while you take Ciprofloxacin Tablets USP or other fluoroquinolones may increase your risk of central nervous system effects and seizures. See “What are the possible side effects of Ciprofloxacin Tablets USP?”
- a blood thinner (warfarin, Coumadin®, Jantoven®)
- tizanidine (Zanaflex®). You should not take Ciprofloxacin Tablets USP if you are already taking tizanidine. See “Who should not take Ciprofloxacin Tablets USP?”
- theophylline (Theo-24®, Elixophyllin®, Theochron®, Uniphyl®, Theolair®)
- glyburide (Micronase®, Glynase®, Diabeta®, Glucovance®). See “What are the possible side effects of Ciprofloxacin Tablets USP?”
- phenytoin (Fosphenytoin Sodium®, Cerebyx®, Dilantin-125®, Dilantin®, Extended Phenytoin Sodium®, Prompt Penytoin Sodium®, Phenytek®)
- products that contain caffeine
- a medicine to control your heart rate or rhythm (antiarrhythmics) See “What are the possible side effects of Ciprofloxacin Tablets USP?”
- an anti-psychotic medicine
- a tricyclic antidepressant
- a water pill (diuretic)
- a steroid medicine. Corticosteroids taken by mouth or by injection may increase the chance of tendon injury. See “What is the most important information I should know about Ciprofloxacin Tablets USP?”
- methotrexate (Trexall®)
- Probenecid (Probalan®, Col-probenecid®)
- Metoclopromide (Reglan®, Reglan ODT®)
- Certain medicines may keep Ciprofloxacin Tablets USP from working correctly. Take Ciprofloxacin Tablets USP either 2 hours before or 6 hours after taking these products:
  - an antacid, multivitamin, or other product that has magnesium, calcium, aluminum, iron, or zinc
  - sucralfate (Carafate®)
  - didanosine (Videx®, Videx EC®)

Ask your healthcare provider if you are not sure if any of your medicines are listed above.

Know the medicines you take. Keep a list of your medicines and show it to your healthcare provider and pharmacist when you get a new medicine.

How should I take Ciprofloxacin Tablets USP?

- Take Ciprofloxacin Tablets USP exactly as prescribed by your healthcare provider.
- Take Ciprofloxacin Tablets USP in the morning and evening at about the same time each day. Swallow the tablet whole. Do not split, crush or chew the tablet. Tell your healthcare provider if you can not swallow the tablet whole.
- Ciprofloxacin Tablets USP can be taken with or without food.
- Ciprofloxacin Tablets USP should not be taken with dairy products (like milk or yogurt) or calcium-fortified juices alone, but may be taken with a meal that contains these products.
- Drink plenty of fluids while taking Ciprofloxacin Tablets USP.
- Do not skip any doses, or stop taking Ciprofloxacin Tablets USP even if you begin to feel better, until you finish your prescribed treatment, unless:
  - you have tendon effects (see “What is the most important information I should know about Ciprofloxacin Tablets USP?”),
  - you have a serious allergic reaction (see “What are the possible side effects of Ciprofloxacin Tablets USP?”), or
  - your healthcare provider tells you to stop.
- This will help make sure that all of the bacteria are killed and lower the chance that the bacteria will become resistant to Ciprofloxacin Tablets USP. If this happens, Ciprofloxacin Tablets USP and other antibiotic medicines may not work in the future.
- If you miss a dose of Ciprofloxacin Tablets USP, take it as soon as you remember. Do not take two doses at the same time, and do not take more than two doses in one day.
- If you take too much, call your healthcare provider or get medical help immediately.

If you have been prescribed Ciprofloxacin Tablets USP after being exposed to anthrax:

- Ciprofloxacin Tablets USP has been approved to lessen the chance of getting anthrax disease or worsening of the disease after you are exposed to the anthrax bacteria germ.
- Take Ciprofloxacin Tablets USP exactly as prescribed by your healthcare provider. Do not stop taking Ciprofloxacin Tablets USP without talking with your healthcare provider. If you stop taking Ciprofloxacin Tablets USP too soon, it may not keep you from getting the anthrax disease.
- Side effects may happen while you are taking Ciprofloxacin Tablets USP. When taking your Ciprofloxacin Tablets USP to prevent anthrax infection, you and your healthcare provider should talk about whether the risks of stopping Ciprofloxacin Tablets USP too soon are more important than the risks of side effects with Ciprofloxacin Tablets USP.
- If you are pregnant, or plan to become pregnant while taking Ciprofloxacin Tablets USP, you and your healthcare provider should decide whether the benefits of taking Ciprofloxacin Tablets USP for anthrax are more important than the risks.

What should I avoid while taking Ciprofloxacin Tablets USP?

- Ciprofloxacin Tablets USP can make you feel dizzy and lightheaded. Do not drive, operate machinery, or do other activities that require mental alertness or coordination until you know how Ciprofloxacin Tablets USP affects you.
- Avoid sunlamps, tanning beds, and try to limit your time in the sun. Ciprofloxacin Tablets USP can make your skin sensitive to the sun (photosensitivity) and the light from sunlamps and tanning beds. You could get severe sunburn, blisters or swelling of your skin. If you get any of these symptoms while taking Ciprofloxacin Tablets USP, call your healthcare provider right away. You should use a sunscreen and wear a hat and clothes that cover your skin if you have to be in sunlight.

What are the possible side effects of Ciprofloxacin Tablets USP?

- Ciprofloxacin Tablets USP can cause side effects that may be serious or even cause death. See “What is the most important information I should know about Ciprofloxacin Tablets USP?”

Other serious side effects of Ciprofloxacin Tablets USP include:

- Central Nervous System effects: Seizures have been reported in people who take fluoroquinolone antibiotics including Ciprofloxacin Tablets USP. Tell your healthcare provider if you have a history of seizures. Ask your healthcare provider whether taking Ciprofloxacin Tablets USP will change your risk of having a seizure.
  Central Nervous System (CNS) side effects may happen as soon as after taking the first dose of Ciprofloxacin Tablets USP. Talk to your healthcare provider right away if you get any of these side effects, or other changes in mood or behavior:
  - feel dizzy
  - seizures
  - hear voices, see things, or sense things that are not there (hallucinations)
  - feel restless
  - tremors
  - feel anxious or nervous
  - confusion
  - depression
  - trouble sleeping
  - nightmares
  - feel more suspicious (paranoia)
  - suicidal thoughts or acts
- Serious allergic reactions: Allergic reactions can happen in people taking fluoroquinolones, including Ciprofloxacin Tablets USP, even after only one dose. Stop taking Ciprofloxacin Tablets USP and get emergency medical help right away if you get any of the following symptoms of a severe allergic reaction:
  - hives
  - trouble breathing or swallowing
  - swelling of the lips, tongue, face
  - throat tightness, hoarseness
  - rapid heartbeat
  - faint
  - yellowing of the skin or eyes. Stop taking Ciprofloxacin Tablets USP and tell your healthcare provider right away if you get yellowing of your skin or white part of your eyes, or if you have dark urine. These can be signs of a serious reaction to Ciprofloxacin Tablets USP (a liver problem).
- Skin rash
  Skin rash may happen in people taking Ciprofloxacin Tablets USP even after only one dose. Stop taking Ciprofloxacin Tablets USP at the first sign of a skin rash and call your healthcare provider. Skin rash may be a sign of a more serious reaction to Ciprofloxacin Tablets USP.
- Serious heart rhythm changes (QT prolongation and torsade de pointes)
  Tell your healthcare provider right away if you have a change in your heart beat (a fast or irregular heartbeat), or if you faint. Ciprofloxacin Tablets USP may cause a rare heart problem known as prolongation of the QT interval. This condition can cause an abnormal heartbeat and can be very dangerous. The chances of this event are higher in people:
  - who are elderly
  - with a family history of prolonged QT interval
  - with low blood potassium (hypokalemia)
  - who take certain medicines to control heart rhythm (antiarrhythmics)
- Intestine infection (Pseudomembranous colitis)
  Pseudomembranous colitis can happen with most antibiotics, including Ciprofloxacin Tablets USP. Call your healthcare provider right away if you get watery diarrhea, diarrhea that does not go away, or bloody stools. You may have stomach cramps and a fever. Pseudomembranous colitis can happen 2 or more months after you have finished your antibiotic.
- Changes in sensation and possible nerve damage (Peripheral Neuropathy)
  Damage to the nerves in arms, hands, legs, or feet can happen in people who take fluoroquinolones, including Ciprofloxacin Tablets USP. Talk with your healthcare provider right away if you get any of the following symptoms of peripheral neuropathy in your arms, hands, legs, or feet:
  Ciprofloxacin tablets may need to be stopped to prevent permanent nerve damage.
  - pain
  - burning
  - tingling
  - numbness
  - weakness
- Low blood sugar (hypoglycemia)
  People who take Ciprofloxacin Tablets USP and other fluoroquinolone medicines with the oral anti-diabetes medicine glyburide (Micronase, Glynase, Diabeta, Glucovance) can get low blood sugar (hypoglycemia) which can sometimes be severe. Tell your healthcare provider if you get low blood sugar with CIPRO. Your antibiotic medicine may need to be changed.
- Sensitivity to sunlight (photosensitivity)
  See “What should I avoid while taking Ciprofloxacin Tablets USP?”
- Joint Problems
  Increased chance of problems with joints and tissues around joints in children under 18 years old. Tell your child’s healthcare provider if your child has any joint problems during or after treatment with Ciprofloxacin Tablets USP.
  The most common side effects of Ciprofloxacin Tablets USP include:
  - nausea
  - headache
  - diarrhea
  - vomiting
  - vaginal yeast infection
  - changes in liver function tests
  - pain or discomfort in the abdomen

These are not all the possible side effects of Ciprofloxacin Tablets USP. Tell your healthcare provider about any side effect that bothers you, or that does not go away.

Call your doctor for medical advice about side effects. You may report side effects to FDA at 1-800-FDA-1088.

How should I store Ciprofloxacin Tablets USP?

- Store Ciprofloxacin Tablets USP below 86°F (30°C)

Keep Ciprofloxacin Tablets USP and all medicines out of the reach of children.

General Information about Ciprofloxacin Tablets USP

Medicines are sometimes prescribed for purposes other than those listed in a Medication Guide. Do not use Ciprofloxacin Tablets USP for a condition for which it is not prescribed. Do not give Ciprofloxacin Tablets USP to other people, even if they have the same symptoms that you have. It may harm them.

This Medication Guide summarizes the most important information about Ciprofloxacin Tablets USP. If you would like more information about CIPRO, talk with your healthcare provider. You can ask your healthcare provider or pharmacist for information about Ciprofloxacin Tablets USP that is written for healthcare professionals.

For more information 1-(866)-562-4597

What are the ingredients in Ciprofloxacin Tablets USP?

- Active ingredient: ciprofloxacin
- Inactive ingredients: pregelatinized starch, microcrystalline cellulose, colloidal silicon dioxide, crospovidone, magnesium stearate, hypromellose, titanium dioxide, polyethylene glycol and purified water

This Medication Guide has been approved by the U.S. Food and Drug Administration.

Manufactured by:
Unique Pharmaceutical Laboratories
(A Div. of J. B. Chemicals & Pharmaceuticals Ltd.),
Mumbai 400 030, India

Distributed by:
Rising Pharmaceuticals, Inc.
Saddle Brook, NJ 07663

Repackaged by:
Proficient Rx LP
Thousand Oaks, CA 91320